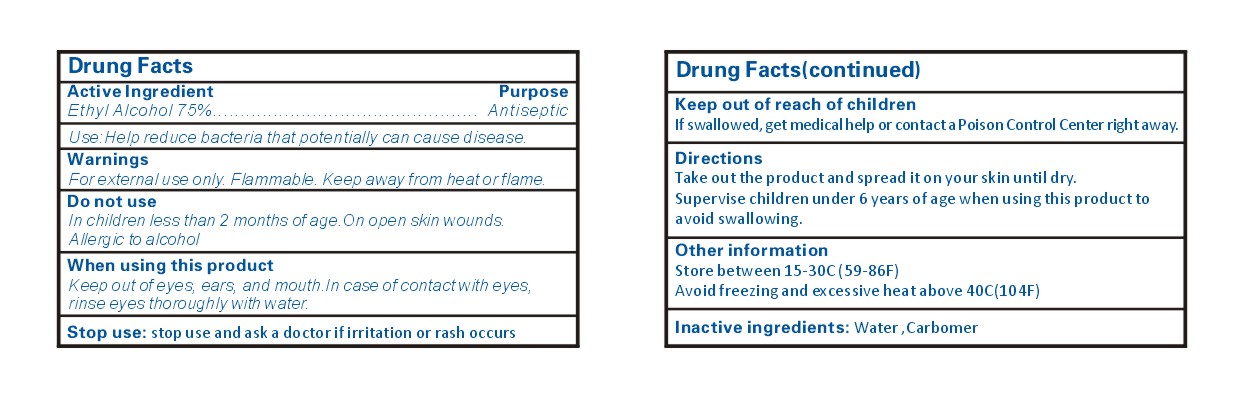 DRUG LABEL: Hand Sanitizer
NDC: 78019-800 | Form: GEL
Manufacturer: Wenzhou Shengkai Technology Industry Co.,  Ltd.
Category: otc | Type: HUMAN OTC DRUG LABEL
Date: 20210202

ACTIVE INGREDIENTS: ALCOHOL 75 mL/100 mL
INACTIVE INGREDIENTS: WATER; CARBOMER HOMOPOLYMER, UNSPECIFIED TYPE

78019-800 75% Alcohol Hand Sanitizer

Active Ingredient

Ethy Alcohol 75%

Purpose

Antiseptic

Use

Use:Help reduce bacteria that potentially can cause disease.

WARNINGS

For externaluse on/y. Flammable. Keep away from heat o1 flame.
Do not use
In children less than 2 months of age On open skin wounds.
Allergic to alcohol
When using this product
Keep out ofeyes, ears, and mouth./n case of contact with eyes,
rinse eyes thoroughly with water.
Stop use: stop use and ask a doctor if irritation or rash occurs

Keep out of reach of children
If swallowed , get medical help or contact a Poison Control Center right away

Directions

Take out the product and spread it on your skin until dry.
Supervise children under 6 years of age when using this product to
avoid swallowing.

Inactive ingredients

Water, Carbomer